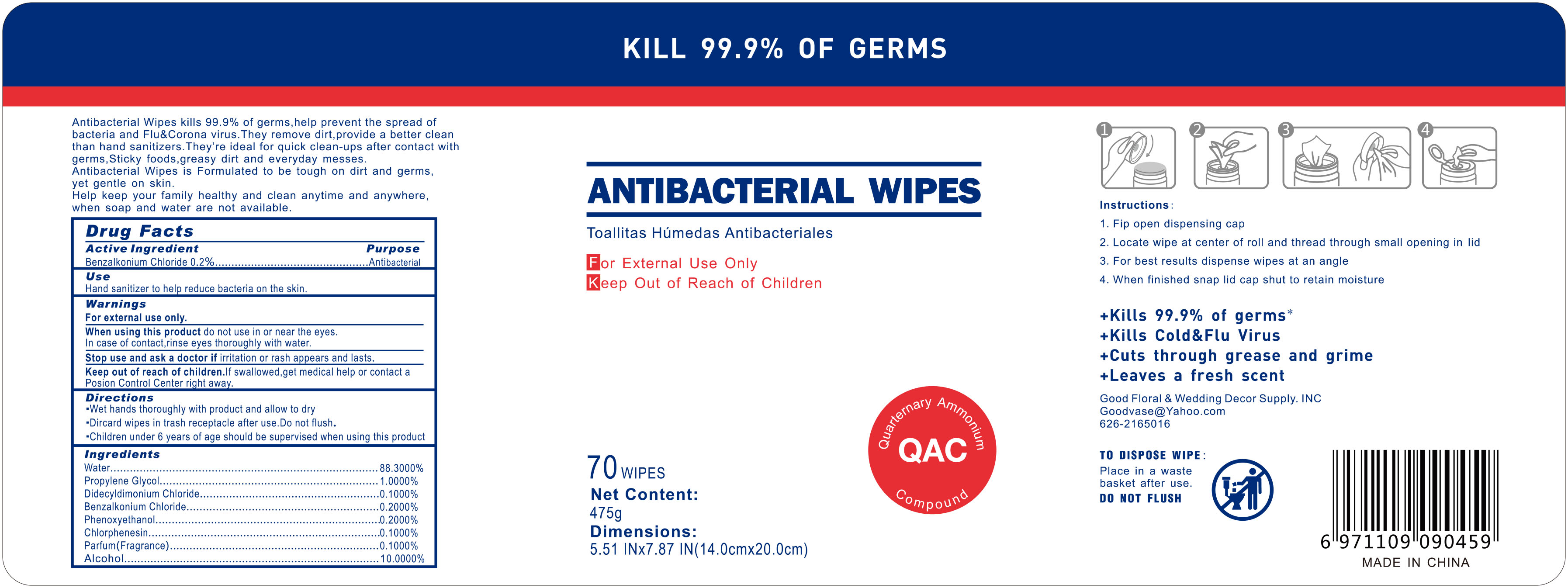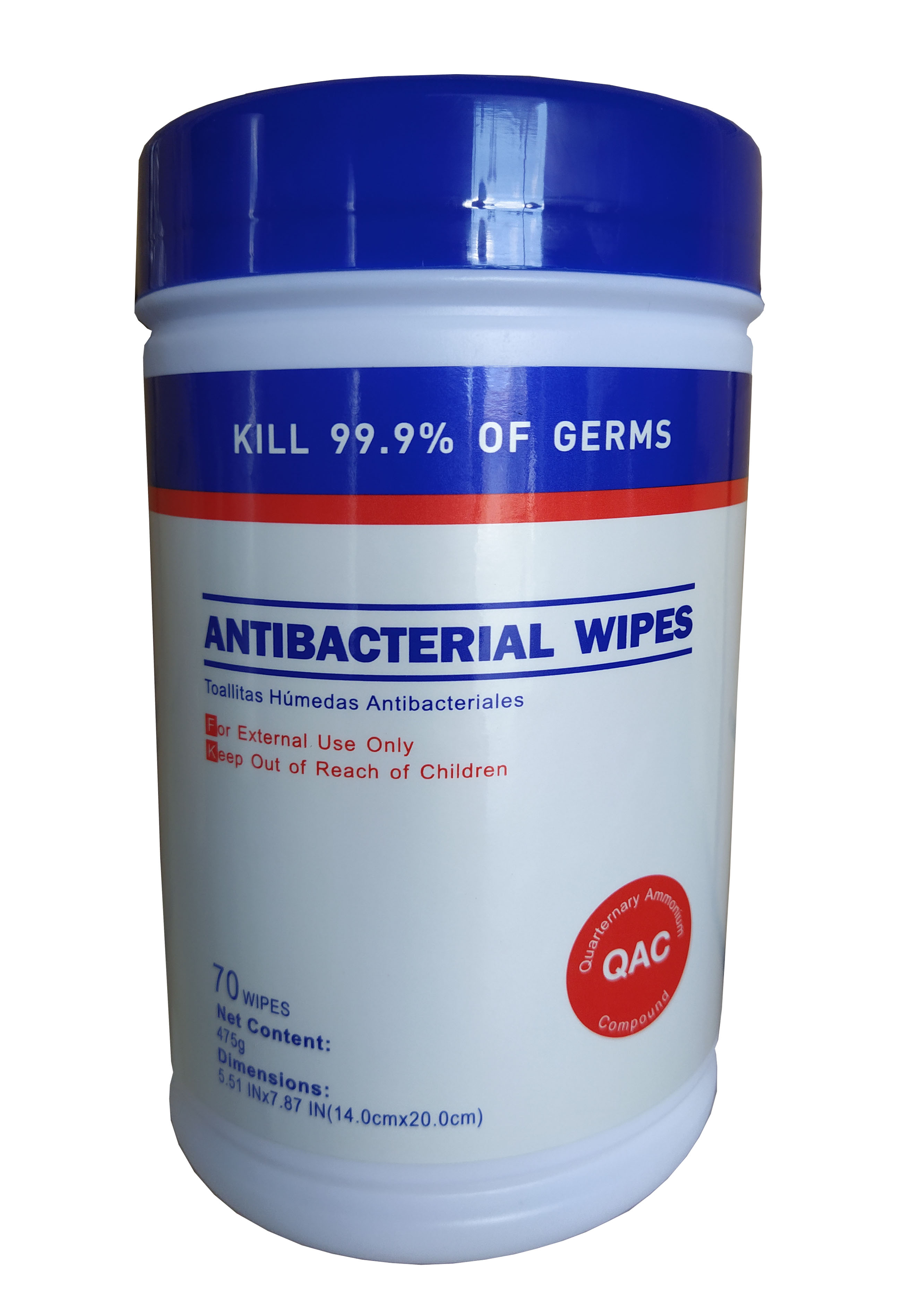 DRUG LABEL: ANTIBACTERIAL WIPES
NDC: 76635-009 | Form: CLOTH
Manufacturer: Hangzhou Glamcos Biotech CO.,LTD
Category: otc | Type: HUMAN OTC DRUG LABEL
Date: 20231123

ACTIVE INGREDIENTS: BENZALKONIUM CHLORIDE 0.2 g/100 g
INACTIVE INGREDIENTS: ALCOHOL; FRAGRANCE LAVENDER & CHIA F-153480; CHLORPHENESIN; DIDECYLDIMONIUM CHLORIDE; WATER; PROPYLENE GLYCOL; PHENOXYETHANOL

Active Ingredient

Benzalkonium Chloride 0.2%

Purpose

Antibacterial

Use

Hand sanitizer to help reduce bacteria on the skin.

Warnings

For external use only.
When using this product do not use in or near the eyes. In case of eye contact, rinse eyes with water.
Stop use and ask a doctor if irritation or rash appears and lasts.
Keep out of reach of children .If swallowed,get medical help or contact a Posion control Center right away.

Keep out of reach of children .If swallowed,get medical help or contact a Posion control Center right away.

Directions

Wet hands thoroughly with product and allow to dry.
Dircard wipes in trash receptacle after use.Do not flush.
Children under 6 years of age should be supervised when using the product.

OTHER SAFETY INFORMATION

1.Fip open dispensing cap
2.Locate wipe at center of roll and thread tyrough small opening in lid
3.For best results dispense wipes at an angle
4.When finished snap lid cap shut to retain moisture

Good Floral & Wedding Decor Supply.INC
Goodvase@Yahoo.com
626-2165016

Inactive Ingredients

Water………………………………….……….88.3000%
Propylene Glycol………………...……………1.0000%
DidecyldimoniumChloride……………………0.1000%
Phenoxyethanol…………………………........0.2000%
Chlorphenesin…………………………………0.1000%
Parfum(Fragrance)……………………………0.1000%

Alcohol……………… ………………………..10.0000%